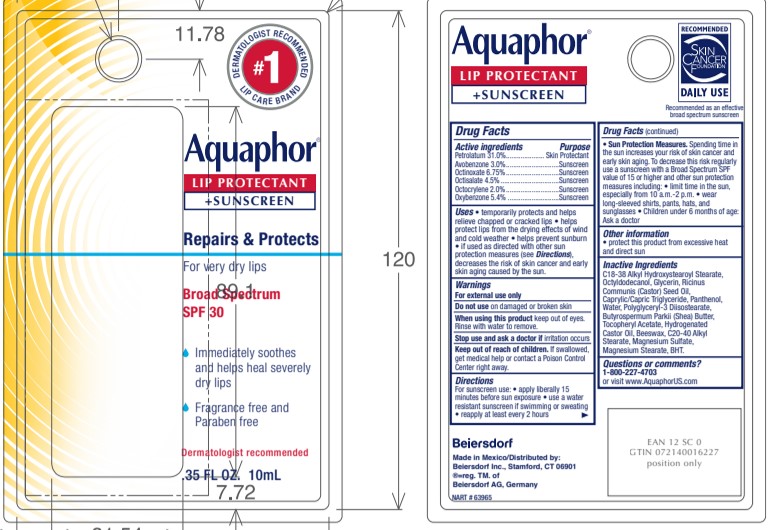 DRUG LABEL: Aquaphor Lip Protectant and Sunscreen
NDC: 10356-111 | Form: LOTION
Manufacturer: Beiersdorf Inc
Category: otc | Type: HUMAN OTC DRUG LABEL
Date: 20251215

ACTIVE INGREDIENTS: PETROLATUM 31 g/100 mL; AVOBENZONE 3 g/100 mL; OCTINOXATE 6.75 g/100 mL; OCTISALATE 4.5 g/100 mL; OCTOCRYLENE 2 g/100 mL; OXYBENZONE 5.4 g/100 mL
INACTIVE INGREDIENTS: OCTYLDODECANOL; GLYCERIN; CASTOR OIL; PANTHENOL; WATER; POLYGLYCERYL-3 DIISOSTEARATE; SHEA BUTTER; ALPHA-TOCOPHEROL ACETATE; HYDROGENATED CASTOR OIL; YELLOW WAX; MAGNESIUM SULFATE, UNSPECIFIED; MAGNESIUM STEARATE; BUTYLATED HYDROXYTOLUENE; MEDIUM-CHAIN TRIGLYCERIDES

Aquaphor Lip Protectant and Sunscreen

Active ingredients
Petrolatum 31.0%
Avobenzone 3.0%
Octinoxate 6.75%
Octisalate 4.5%
Octocrylene 2.0%
Oxybenzone 5.4%

Purpose
Skin Protectant
Sunscreen

Uses
•temporarily protects and helps relieve chapped or cracked lips
•helps protect lips from the drying effects of wind and cold weather
•helps prevent sunburn
•if used as directed with other sun protection measures (see Directions), decreases the risk of skin cancer and early skin aging caused
by the sun

Warnings
For external use only

Do not use on damaged or broken skin

When using this product avoid contact with eyes. Rinse with water to remove.

Stop use and ask a doctor if irritation occurs

Keep out of reach of children. If swallowed, get medical help or contact a
Poison Control Center right away

Directions
For sunscreen use: •apply liberally 15 minutes before sun exposure •reapply at least
every 2 hours •use a water resistant sunscreen if swimming or sweating
• Sun Protection Measures.
Spending time in the sun increases your risk of skin cancer and early skin aging. To decrease this risk,
regularly use a sunscreen with a Broad Spectrum SPF value of 15 or higher and other sun protection
measures including: •limit time in the sun, especially from 10 a.m. - 2 p.m. •wear long-sleeved shirts,
pants, hats, and sunglasses
•children under 6 months of age: ask a doctor

INACTIVE INGREDIENT

Inactive ingredients C18-38 Alkyl Hydroxystearoyl Stearate, Octyldodecanol, Glycerin, Ricinus
Communis (Castor) Seed Oil, Caprylic/Capric Triglyceride, Panthenol, Water, Polyglyceryl-3 Diisostearate,
Butyrospermum Parkii (Shea) Butter, Tocopheryl Acetate, Hydrogenated Castor Oil, Beeswax, C20-40 Alkyl
Stearate, Magnesium Sulfate, Magnesium Stearate, BHT.

Questions

800-227-4703

PACKAGE LABEL

Aquaphor Lip Protectant + Sunscreen

Repairs and Protects

For severly dry lips

Broad Spectrum SPF 30

Immediately soothes and helps heal severely dry lips
Fragrance free and Paraben free.